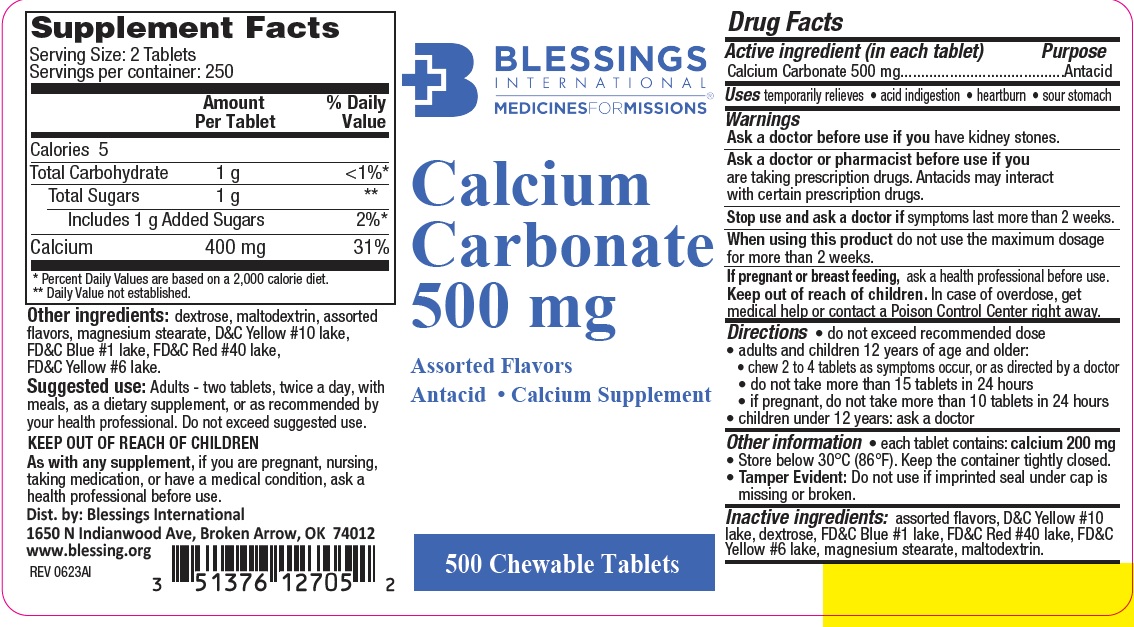 DRUG LABEL: CALCIUM CARBONATE
NDC: 51376-127 | Form: TABLET, CHEWABLE
Manufacturer: Blessings International
Category: otc | Type: HUMAN OTC DRUG LABEL
Date: 20231025

ACTIVE INGREDIENTS: CALCIUM CARBONATE 500 mg/1 1
INACTIVE INGREDIENTS: DEXTROSE; MALTODEXTRIN; D&C YELLOW NO. 10; FD&C YELLOW NO. 6; FD&C RED NO. 40; FD&C BLUE NO. 1; MAGNESIUM STEARATE

763-BLE

Active ingredient (in each tablet)

Calcium Carbonate 500 mg

Purpose

Antacid

Uses

temporarily relieves:

- acid indigestion
- heartburn
- sour stomach

Warnings

Ask a doctor before use if you have kidney stones.

Ask a doctor before use if you are taking prescription drugs. Antacids may interact with certain prescription drugs.

Stop use and ask a doctor if symptoms last more than 2 weeks.

When using this product do not use the maximum dosage for more than 2 weeks

If pregnant or breast feeding, ask a health professional before use.

Keep out of reach of children. In case of overdose, get medical help or contact a Poison Control Center right away.

Directions

• do not exceed recommended dose
• adults and children 12 years of age and older:
• chew 2 to 4 tablets as symptoms occur, or as directed by a doctor
• do not take more than 15 tablets in 24 hours
• if pregnant, do not take more than 10 tablets in 24 hours
• children under 12 years: ask a doctor

Other information

- each tablet contains: calcium 200 mg
- Store below 30°C (86°F). Keep the container tightly closed.
- Tamper Evident: Do not use if imprinted seal under cap is
  missing or broken.

Inactive ingredients

assorted flavors, D&C Yellow #10 lake, dextrose, FD&C Blue #1 lake, FD&C Red #40 lake, FD&C Yellow #6 lake, magnesium stearate, maltodextrin